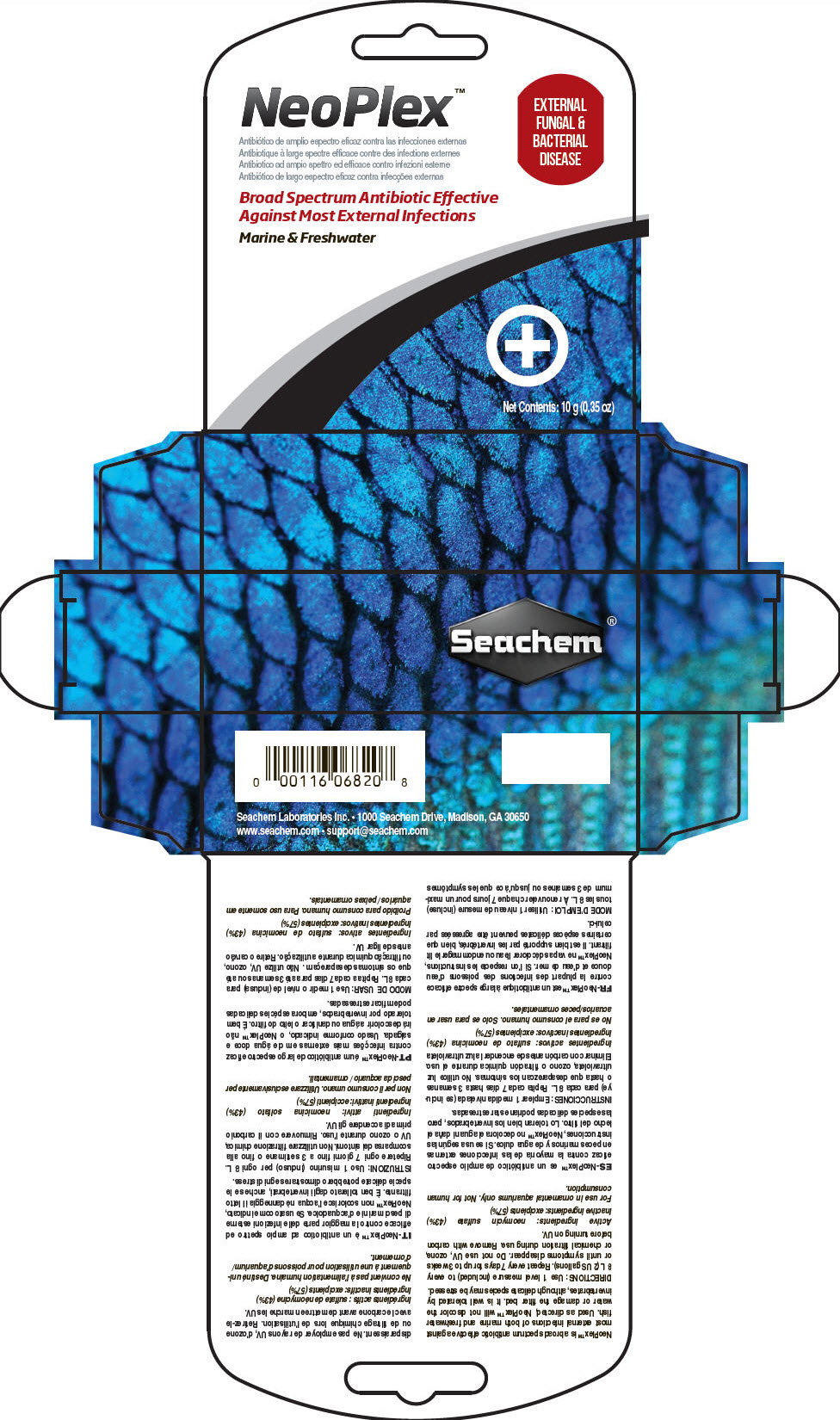 DRUG LABEL: Neoplex
NDC: 55999-069 | Form: POWDER
Manufacturer: Seachem Laboratories Inc.
Category: animal | Type: OTC ANIMAL DRUG LABEL
Date: 20180716

ACTIVE INGREDIENTS: Neomycin Sulfate 425 mg/1 g

Neoplex™

VETERINARY INDICATIONS

NeoPlex™ is a broad spectrum antibiotic effective against most external infections of both marine and freshwater fish. Used as directed, NeoPlex™ will not discolor the water or damage the filter bed. It is well tolerated by invertebrates, although delicate species may be stressed.

DOSAGE AND ADMINISTRATION

DIRECTIONS: Use 1 level measure (included) to every 8 L (2 US gallons). Repeat every 7 days for up to 3 weeks or until symptoms disappear. Do not use UV, ozone, or chemical filtration during use. Remove with carbon before turning on UV.

Active ingredients: neomycin sulfate (43%)

Inactive ingredients: excipients (57%)

SAFE HANDLING WARNING

For use in ornamental aquariums only. Not for human consumption.

Seachem Laboratories Inc. • 1000 Seachem Drive, Madison, GA 30650

www.seachem.com • support@seachem.com

PRINCIPAL DISPLAY PANEL - 10 g Vial Carton

NeoPlex™

EXTERNAL
FUNGAL &
BACTERIAL
DISEASE

Broad Spectrum Antibiotic Effective
Against Most External Infections

Marine & Freshwater

Net Contents: 10 g (0.35 oz)

Seachem®